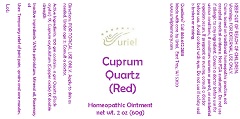 DRUG LABEL: Cuprum Quartz (Red)
NDC: 48951-3152 | Form: OINTMENT
Manufacturer: Uriel Pharmacy Inc.
Category: homeopathic | Type: HUMAN OTC DRUG LABEL
Date: 20181211

ACTIVE INGREDIENTS: SILICON DIOXIDE 1 [hp_X]/1 g; CUPRIC OXIDE 1 [hp_X]/1 g
INACTIVE INGREDIENTS: PETROLATUM; MINERAL OIL; ROSEMARY OIL

Cuprum Quartz (Red)

INDICATIONS AND USAGE

Directions: FOR TOPICAL USE ONLY.

DOSAGE AND ADMINISTRATION

Apply to skin as needed. Under age 2: Consult a doctor.

ACTIVE INGREDIENT

Active Ingredients: 100 gm contains: 4 gm Quartz (Rock crystal) 1X; Cuprum oxydulatum (Copper oxide) 1X double strength

Inactive Ingredients: White petrolatum, Mineral oil, Rosemary oil

PURPOSE

Uses: Temporary relief of joint pain, sprains and sore muscles.

KEEP OUT OF REACH OF CHILDREN.

Warnings: FOR EXTERNAL USE ONLY.
Claims based on traditional homeopathic practice, not accepted medical evidence. Not FDA evaluated. Do not use if allergic to any ingredient. Consult a doctor before use for serious conditions, if conditions worsen or persist, or accidental ingestion occurs. If pregnant or nursing, consult a doctor before use. Avoid contact with eyes. Do not use if safety seal is broken or missing.

QUESTIONS

Questions? Call 866.642.2858 Made with care by Uriel, East Troy, WI 53120 www.urielpharmacy.com